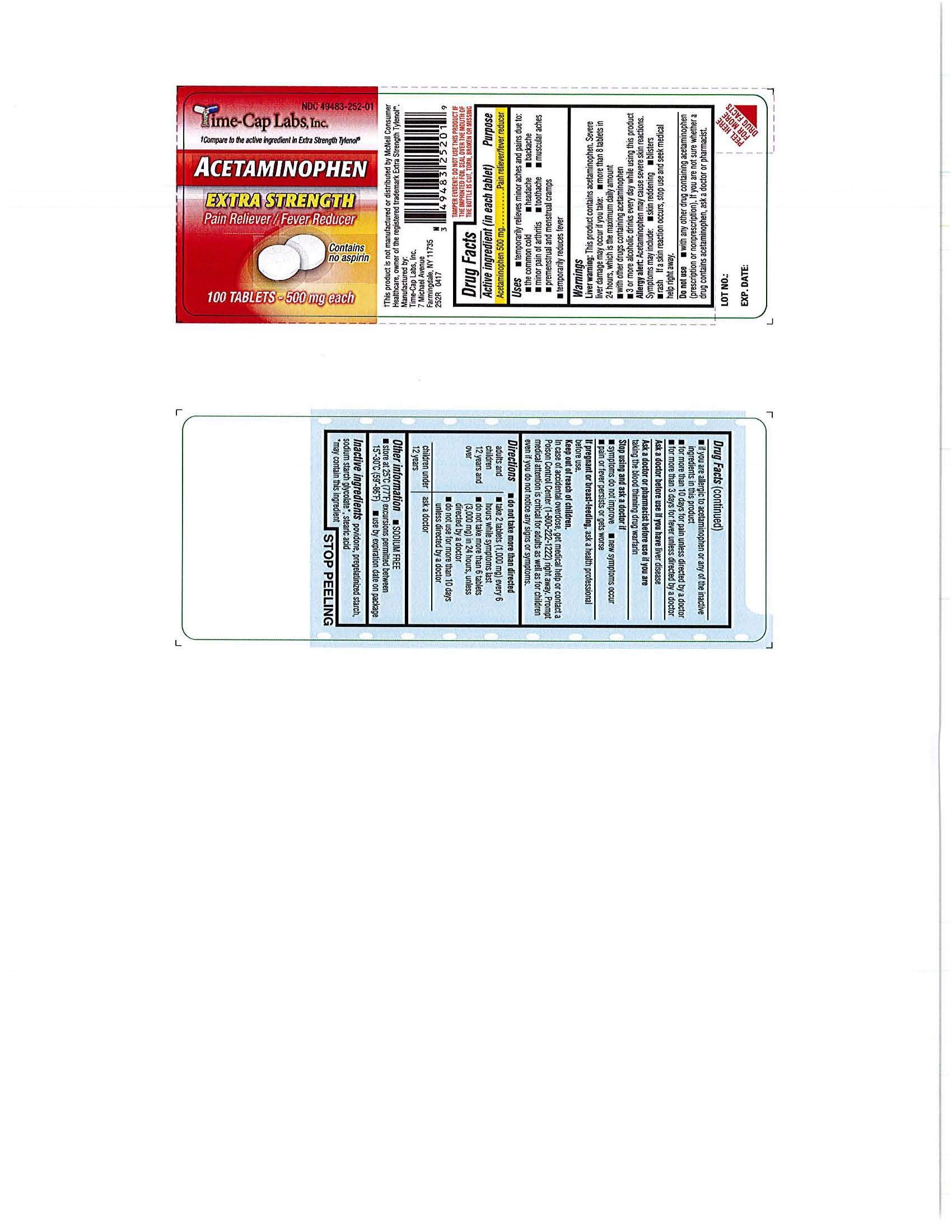 DRUG LABEL: ACETAMINOPHEN
NDC: 49483-252 | Form: TABLET
Manufacturer: TIME CAP LABORATORIES, INC
Category: otc | Type: HUMAN OTC DRUG LABEL
Date: 20191122

ACTIVE INGREDIENTS: ACETAMINOPHEN 500 mg/1 1
INACTIVE INGREDIENTS: POVIDONE; STARCH, CORN; SODIUM STARCH GLYCOLATE TYPE A POTATO; STEARIC ACID

252R - ALLERGY TIME

Active ingredient (in each tablet)

Acetaminophen 500 mg

Purpose

Pain reliever/fever reducer

Uses

- temporarily relieves minor aches and pains due to:
-
  - the common cold
  - headache
  - backache
  - minor pain of arthritis
  - toothache
  - muscular aches
  - premenstrual and menstrual cramps
- temporarily reduces fever

Warnings
Liver warning:

This product contains Acetaminophen. Severe liver damage may occur if you have:

more than 8 tablets in 24 hours, which is the maximum daily amount
with other drugs containing acetaminophen
3 or more alcoholic drinks every day while using this product

Allergy alert: Acetaminophen may cause severe skin reactions. Symptoms may include *skin redding *blisters *rash.

If a skin reaction occurs, stop use and seek medical help right away.

Do not use

- with any other drug containing acetaminophen (prescription or nonprescription). If you are not sure whether a drug contains acetaminophen, ask a doctor or pharmacist.

Ask a doctor before use if you have

- liver disease

Ask a doctor or pharmacist before use if you are

- taking the blood thinning drug warfarin

Stop use and ask a doctor if

- pain gets worse or lasts more than 10 days
- fever gets worse or lasts more than 3 days
- new symptoms occur
- redness or swelling is present

These could be signs of a serious condition.

If pregnant or breast-feeding

, ask a health professional before use.

Keep out of reach of children.

OVERDOSAGE

Overdose warning:

Taking more than the recommended dose (overdose) may cause liver damage. In case of overdose, get medical help or contact a Poison Control Center (1-800-222-1222) right away. Quick medical attention is critical for adults as well as for children even if you do not notice any signs or symptoms.

Directions

- do not take more than directed (see overdose warning)

adults and children 12 years and over

- take 2 tablets (1,000 mg) every 6 hours while symptoms last
- do not take more than 6 tablets (3,000 ng) in 24 hours, unless directed by a doctor
- do not take for more than 10 days unless directed by a doctor

children under 12 years

- do not use this adult extra strength product in children under 12 years of age; this will provide more than the recommended dose (overdose) of acetaminophen and may cause liver damage

Other information

- store at 25°C (77°F) excursions permitted between 15°-30°C (59°-86°F)
- use by expiration date on package

Inactive ingredients

povidone, pregelatinized starch, sodium starch glycolate*, stearic acid
*may contain this ingredient